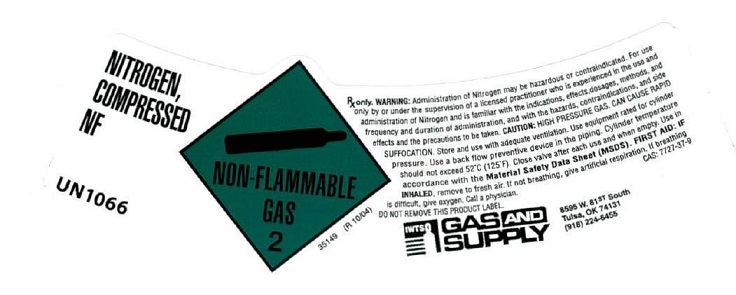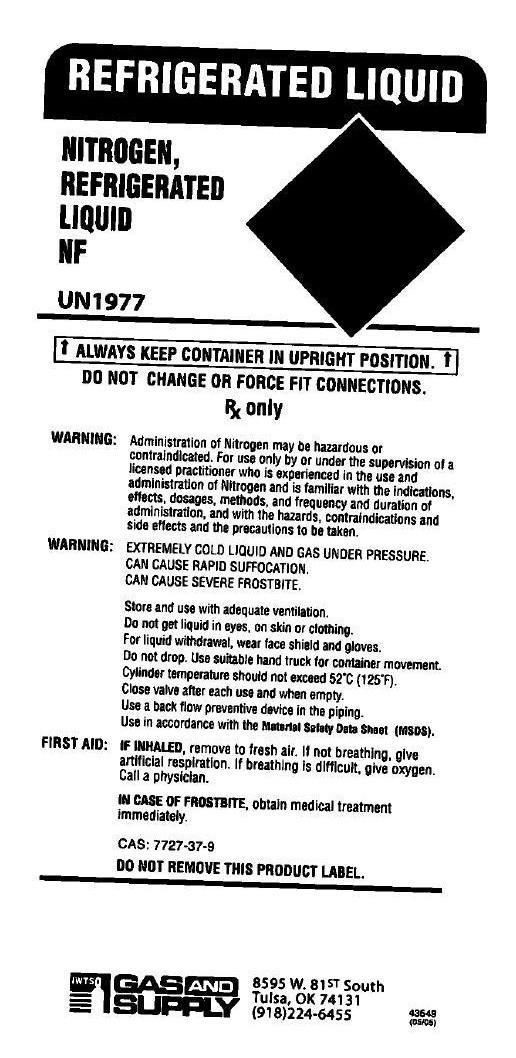 DRUG LABEL: Nitrogen
NDC: 58404-002 | Form: GAS
Manufacturer: Industrial Welding & Tool Supply, Ltd.
Category: prescription | Type: HUMAN PRESCRIPTION DRUG LABEL
Date: 20251208

ACTIVE INGREDIENTS: NITROGEN 995 mL/1 L

Nitrogen

PACKAGE LABEL

NITROGEN, COMPRESSED NF UN1066. NON-FLAMMABLE GAS 2. Rx only. WARNING: Administration of Nitrogen may be hazardous or contraindicated. For use only by or under the supervision of a licensed practitioner who is experienced in the use and administration of Nitrogen and is familiar with the indications, effects, dosages, methods, and frequency and duration of administration, and with the hazards, contraindications, and side effects and the precautions to be taken. CAUTION: HIGH PRESSURE GAS. CAN CAUSE RAPID SUFFOCATION. Store and use with adequate ventilation. Use equipment rated for cylinder pressure. Use a back flow preventive device in the piping. Cylinder temperature should not exceed 52 degrees C (125 degrees F). Close valve after each use and when empty. Use in accordance with the Material Safety Data Sheet (MSDS). FIRST AID: IF INHALED, remove to fresh air. If not breathing, give artificial respiration. If breathing is difficult, give oxygen. Call a physician. CAS: 7727-37-9. DO NOT REMOVE THIS PRODUCT LABEL. GAS AND SUPPLY 8595 W 81ST South. Tulsa, OK 74131 (918) 224-6455

PACKAGE LABEL

REFRIGERATED LIQUID NITROGEN, FREFRIGERATED LIQUID NF. UN 1977. ALWAYS KEEP CONTAINER IN UPRIGHT POSITION. DO NOT CHANGE OR FORCE FIT CONNECTIONS. RX ONLY. WARNING: Administration of Nitrogen may be hazardous or contraindicated. For use only by or under the supervision of a licensed practitioner who is experienced in the use and administration of Nitrogen and is familiar with the indications, effects, dosages, methods, and frequency and duration of administration, and with the hazards, contraindications, and side effects and the precautions to be taken. WARNING: EXTREMELY COLD LIQUID AND GAS UNDER PRESSURE. CAN CAUSE RAPID SUFFOCATION. CAN CAUSE SEVERE FROSTBITE. </content>
<content>Store and use with adequate ventilation. Do not get liquid in eyes, on skin or clothing. For liquid withdrawal, wear face shield and gloves. Do not drop. Use suitable hand truck for container movement. Cylinder temperature should not exceed 52 degrees C (125 degrees F). Close valve after each use and when empty. Use a back flow preventive device in the piping. Use in accordance with the Material Safety Data Sheet (MSDS). FIRST AID: IF INHALED, remove to fresh air. If not breathing, give artificial respiration. If breathing is difficult, give oxygen. Call a physician. IN CASE OF FROSTBITE, obtain medical treatment immediately. CAS: 7727-37-9. DO NOT REMOVE THIS PRODUCT LABEL. GAS AND SUPPLY 8595 W 81ST South. Tulsa, OK 74131 (918) 224-6455